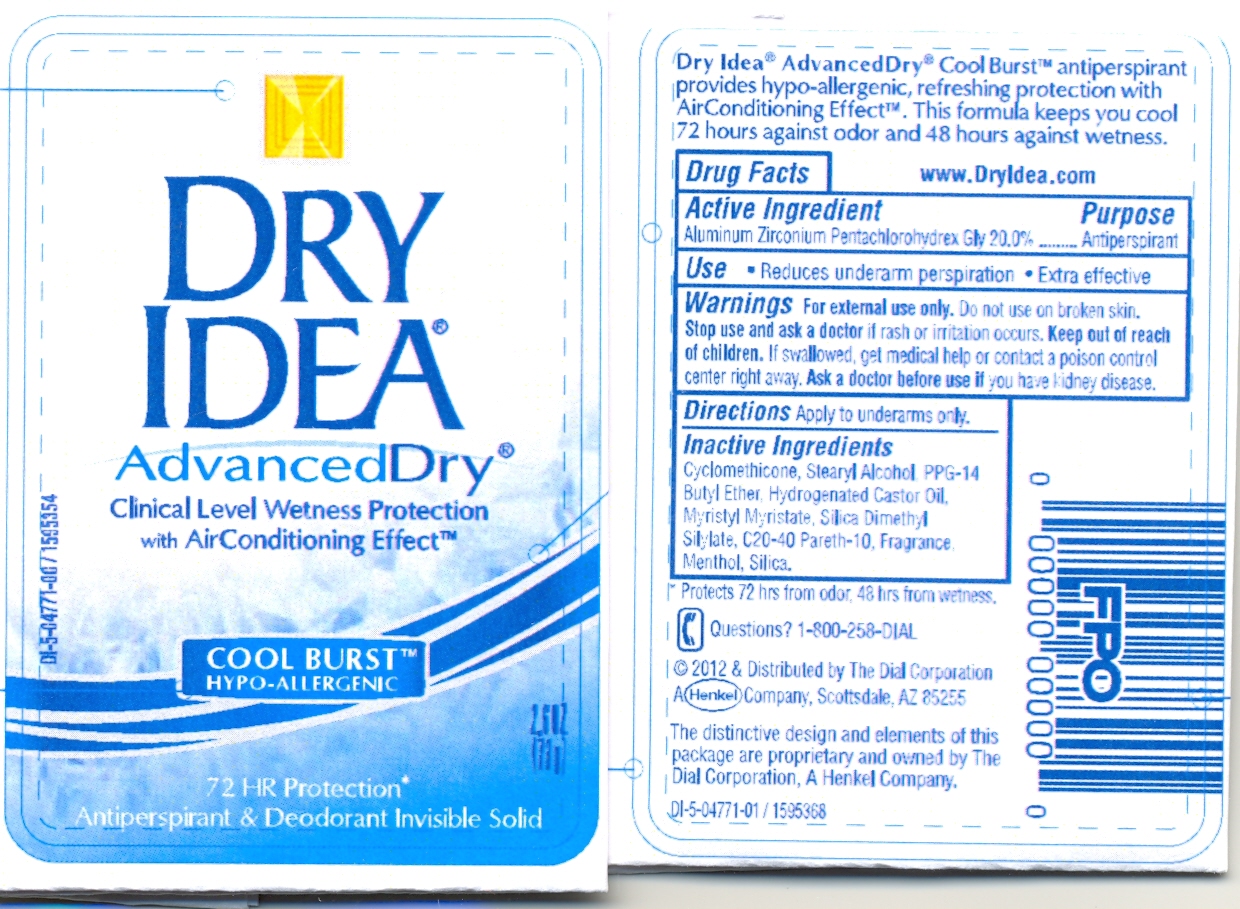 DRUG LABEL: Dry Idea A.Dry Inv.Sol. Antiperspirant Cool Blast
NDC: 54340-771 | Form: STICK
Manufacturer: The Dial Corporation
Category: otc | Type: HUMAN OTC DRUG LABEL
Date: 20111109

ACTIVE INGREDIENTS: Aluminum Zirconium Pentachlorohydrex Gly 15.4 g/73 g
INACTIVE INGREDIENTS: STEARYL ALCOHOL 11.68 g/73 g; PPG-14 Butyl Ether 7.300 g/73 g; HYDROGENATED CASTOR OIL 2.080 g/73 g; SILICON DIOXIDE 2.065 g/73 g; MYRISTYL MYRISTATE 1.460 g/73 g; TALC 0.730 g/73 g; POTASSIUM ALUM 0.073 g/73 g

Dry Idea Advanced Dry Antiperspirant & Deodorant Invisible Solid Cool Burst

ACTIVE INGREDIENT

Aluminum Zirconium Pentachlorohydrex Gly 20.0%.............Antiperspirant

PURPOSE

Use: Reduces underarm perspiration - Extra effective

WARNINGS

Warnings: For external use only. Do not use on broken skin.

Stop use and ask a doctor if rash or irritation occurs.

Keep out of reach of children.

GENERAL PRECAUTIONS

If swallowed, get medical help or contact a poison control center right away.

Ask a doctor before use if you have kidney disease.

DOSAGE AND ADMINISTRATION

Directions Apply to underarms only.

INACTIVE INGREDIENT

Cyclomethicone, Stearyl Alcohol, PPG-14 Butyl Ether, Hydrogenated Castor Oil, Myristyl Myristate, Silica Dimethyl Silylate, Fragrance, C20-40 Pareth-10, Potassium Alum, Talc, Tocopheryl Acetate (Vitamin E Acetate), Silica.

INDICATIONS AND USAGE

Protects 48 Hrs from odor, 24 hours from wetness.

Questions? 1-800-258-DIAL

HOW SUPPLIED

2011 Distributed By The Dial Corporation A Henkel Company, Scottsdale, AZ 85255

The distinctive design and elements of this package are proprietary and owned by The dial Corporation, A Henkel Company. U.S.Pat.No.:5,417,964